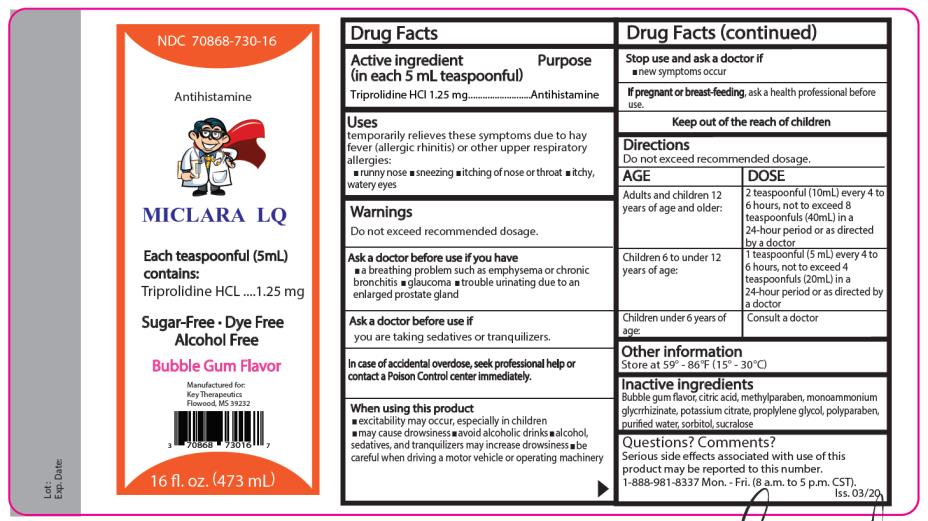 DRUG LABEL: Miclara LQ
NDC: 70868-730 | Form: LIQUID
Manufacturer: Key Therapeutics
Category: otc | Type: HUMAN OTC DRUG LABEL
Date: 20220126

ACTIVE INGREDIENTS: TRIPROLIDINE HYDROCHLORIDE 1.25 mg/5 mL
INACTIVE INGREDIENTS: CITRIC ACID MONOHYDRATE; METHYLPARABEN; AMMONIUM GLYCYRRHIZATE; POTASSIUM CITRATE; PROPYLENE GLYCOL; PROPYLPARABEN; WATER; SORBITOL; SUCRALOSE

Miclara LQ

Miclara LQ- triprolidinehydrochloride liquid

Key Therapeutics

Disclaimer: Most OTC drugs are not reviewed and approved by FDA; however, they may be marketed if they comply with applicable regulations and policies. FDA has not evaluated whether this product complies.

----------

MICLARA LQ LIQUID

Drug Facts

Active ingredients

(in each 5 mL teaspoonful) Triprolidine HCl 1.25 mg

Purpose

Antihistamine

Uses

temporarily relieves these symptoms due to hay fever (allergic rhinitis) or other upper respiratory allergies:

- runny nose
- sneezing
- itching of the nose or throat itchy,
- watery eyes

Warnings

Do not exceed recommended dosage.

Do not use this product if you have

- a breathing problem such as emphysema or chronic bronchitis
- glaucoma
- trouble urinating due to an enlarged prostate gland

Ask a doctor before use

if you are taking sedatives or tranquilizers.

When using this product

- may cause excitability especially in children
- may cause drowsiness
- avoid alcoholic drinks
- alcohol, sedatives, and tranquilizers may increase the drowsiness effect
- be careful when driving a motor vehicle or operating machinery

Stop use and ask a doctor if

- new symptoms occur

If pregnant or breast-feeding, ask a health professional before use.

Keep out of the reach of children.

In case of accidental overdose seek professional help or contact a Poison Control Center immediately.

Directions

Do not exceed recommended dosage.

Adults and children

12 years of age and older:

Children 6 to under 12 years of age:

2 teaspoonfuls (10 mL) every 4 to 6 hours, not to exceed

8 teaspoonfuls (40mL) in 24-hour

period or as directed by a doctor.

1 teaspoonful (5 mL) every 4 to 6 hours, not to exceed 4 teaspoonfuls (20mL) in a 24-hour period or as directed by a doctor.

Children under 6 years of age: Consult a doctor

Other information

Store at 59° - 86°F (15° - 30°C)

Inactive ingredients

Bubble gum flavor, citric acid, methylparaben, monoammonium glycyrrhizinate, potassium citrate, propylene glycol, propylparaben, purified water, sorbitol, sucralose.

Questions? Comments?

Serious side effects associated with use of this product May be reported to this number. Call 1-888-981-8337

Mon - Fri (8 a.m. to 5 p.m. CST)

PRINCIPAL DISPLAY PANEL

NDC 70868-730-16 Miclara LQ

Antihistamine

Each 5 mL (1 teaspoonful) contains: Triprolidine HCl 1.25 mg………Antihistamine

Bubble Gum Flavor

Dye Free - Sugar Free - Alcohol Free

16 fl oz. (473 mL)

Distributed by:

Key Therapeutics, LLC

Flowood, MS 39232

Iss. 03/20